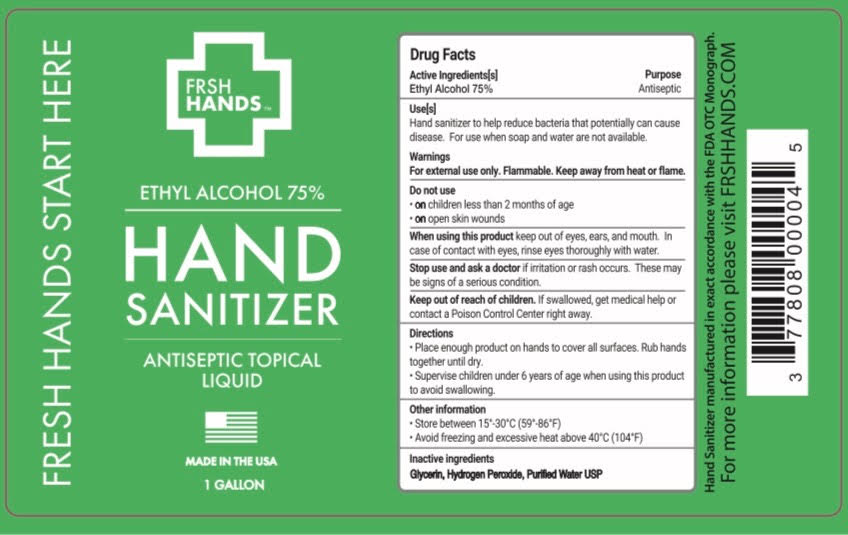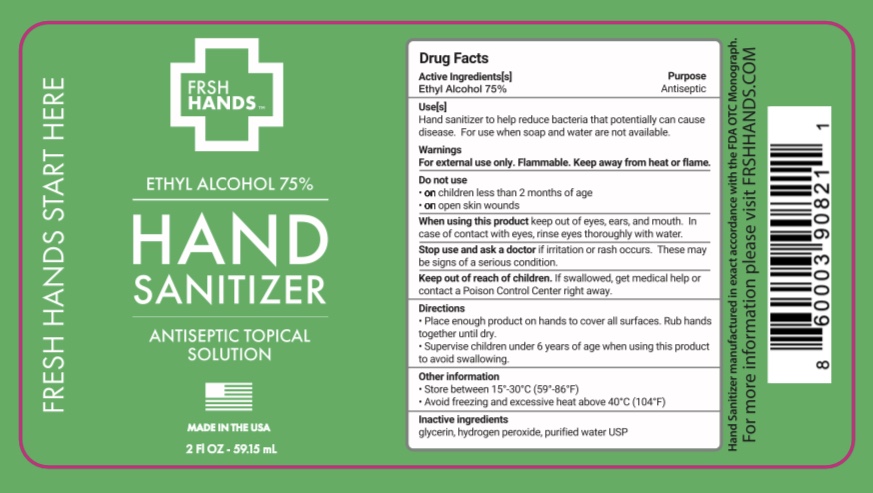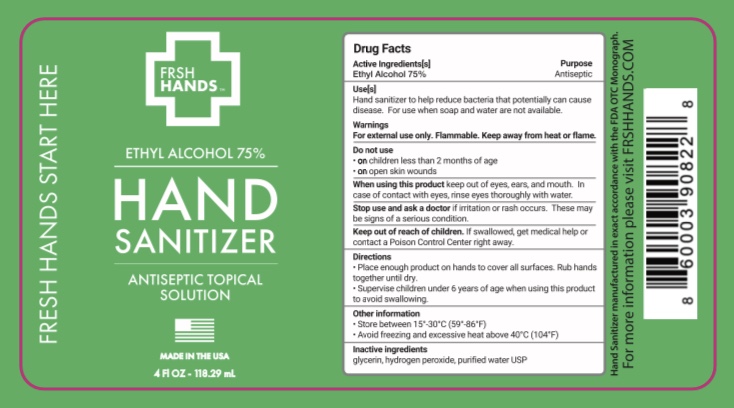 DRUG LABEL: Hand Sanitizer
NDC: 78217-001 | Form: LIQUID
Manufacturer: FRSH HANDS LLC
Category: otc | Type: HUMAN OTC DRUG LABEL
Date: 20200610

ACTIVE INGREDIENTS: ALCOHOL 75 mL/100 mL
INACTIVE INGREDIENTS: HYDROGEN PEROXIDE 0.125 mL/100 mL; GLYCERIN 1.45 mL/100 mL; WATER 23.425 mL/100 mL

ACTIVE INGREDIENT

Ethyl Alcohol 75% v/v.

PURPOSE

Antiseptic

INSTRUCTIONS FOR USE

Hand sanitizer to help reduce bacteria that potentially can cause disease. For use when soap and water are not available.

WARNINGS

For external use only. Flammable. Keep away from heat or flame.

DO NOT USE

- on children less than 2 months of age
- on open skin wounds

When using this product keep out of eyes, ears, and mouth. In case of contact with eyes, rinse eyes thoroughly with water.

Stop use and ask a doctor if irritation or rash occurs. These may be signs of a serious condition.

Keep out of reach of children. If swallowed, get medical help or contact a Poison Control Center right away.

INSTRUCTIONS FOR USE

- Place enough product on hands to cover all surfaces. Rub hands together until dry.
- Supervise children under 6 years of age when using this product to avoid swallowing.

Other information

- Store between 15°- 30°C (59°-86°F)
- Avoid freezing and excessive heat above 40°C (104°F)

INACTIVE INGREDIENT

glycerin, hydrogen peroxide, purified water USP

DOSAGE AND ADMINISTRATION

- Place enough product on hands to cover all surfaces. Rub hands together until dry.
- Supervise children under 6 years of age when using this product to avoid swallowing.

INDICATIONS AND USAGE

Hand sanitizer to help reduce bacteria that potentially can cause disease. For use when soap and water are not available.

Warnings

For external use only. Flammable. Keep away from heat or flame.

PACKAGE LABEL

59.15 mL NDC: 78217-001-01

118.29 mL NDC: 78217-001-02

3785 mL NDC: 78217-001-03